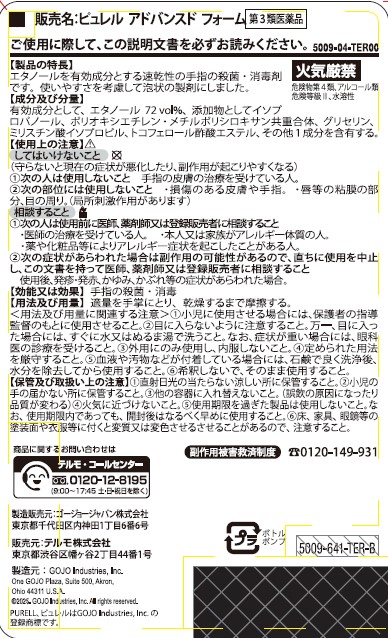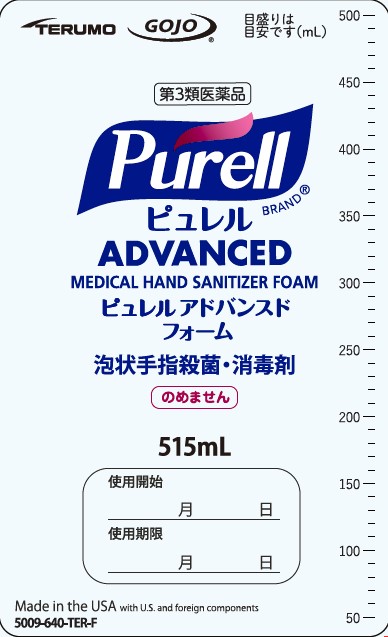 DRUG LABEL: PURELL Advanced Medical Hand Sanitizer Foam
NDC: 21749-038 | Form: LIQUID
Manufacturer: GOJO Industries, Inc.
Category: otc | Type: HUMAN OTC DRUG LABEL
Date: 20251224

ACTIVE INGREDIENTS: ALCOHOL 70 mL/100 mL
INACTIVE INGREDIENTS: WATER; ISOPROPYL ALCOHOL; PEG-12 DIMETHICONE (300 CST); CAPRYLYL GLYCOL; GLYCERIN; ISOPROPYL MYRISTATE; .ALPHA.-TOCOPHEROL ACETATE

PURELL Advanced Medical Hand Sanitizer Foam